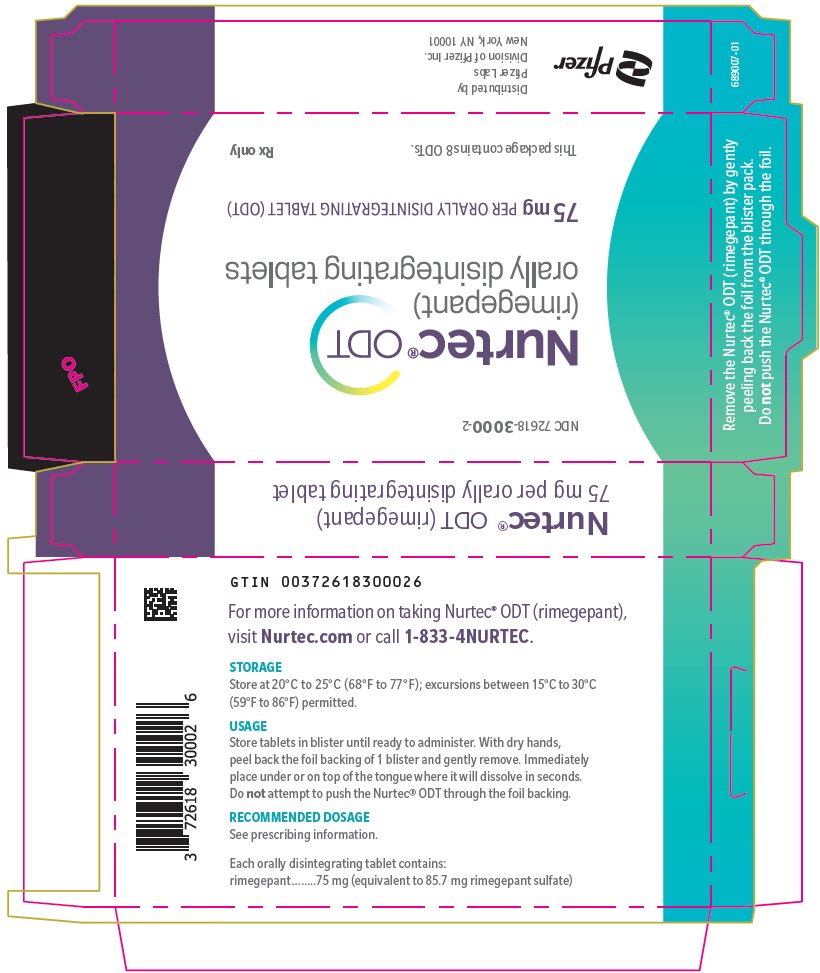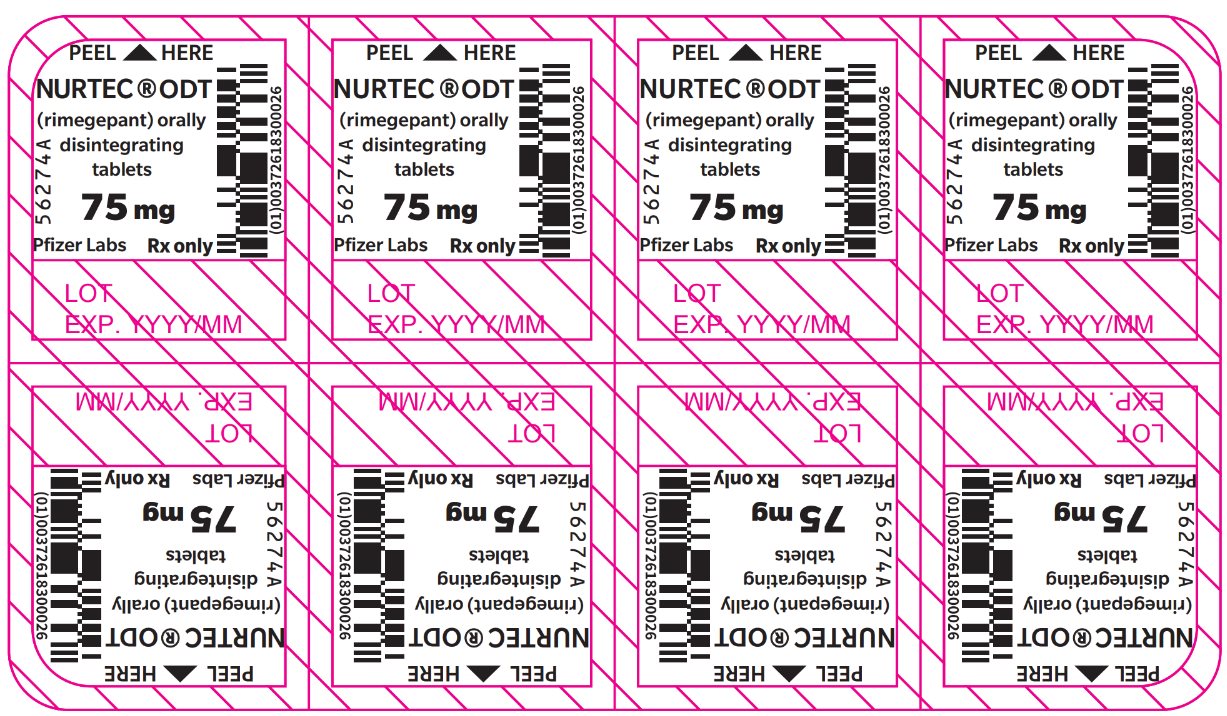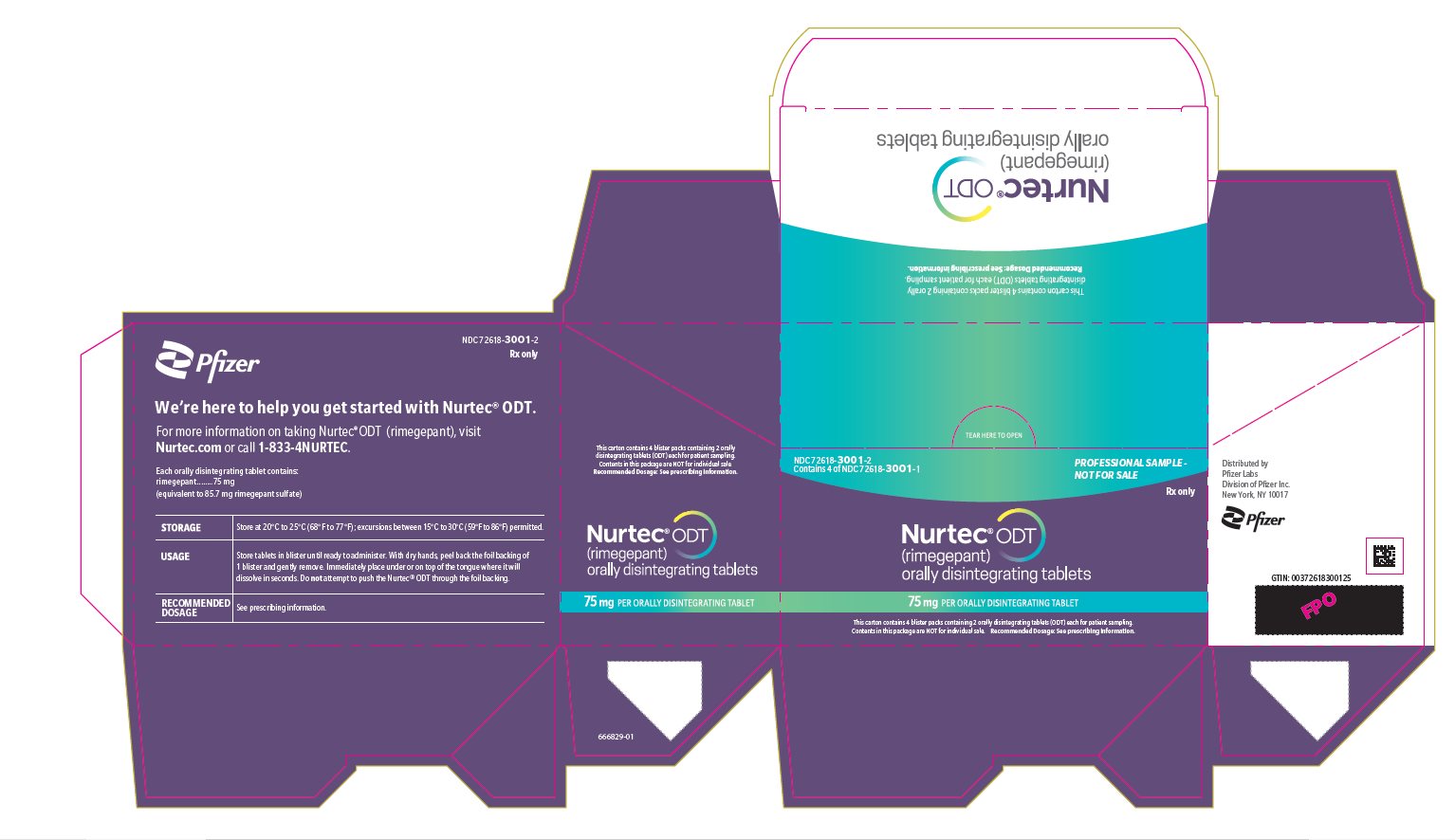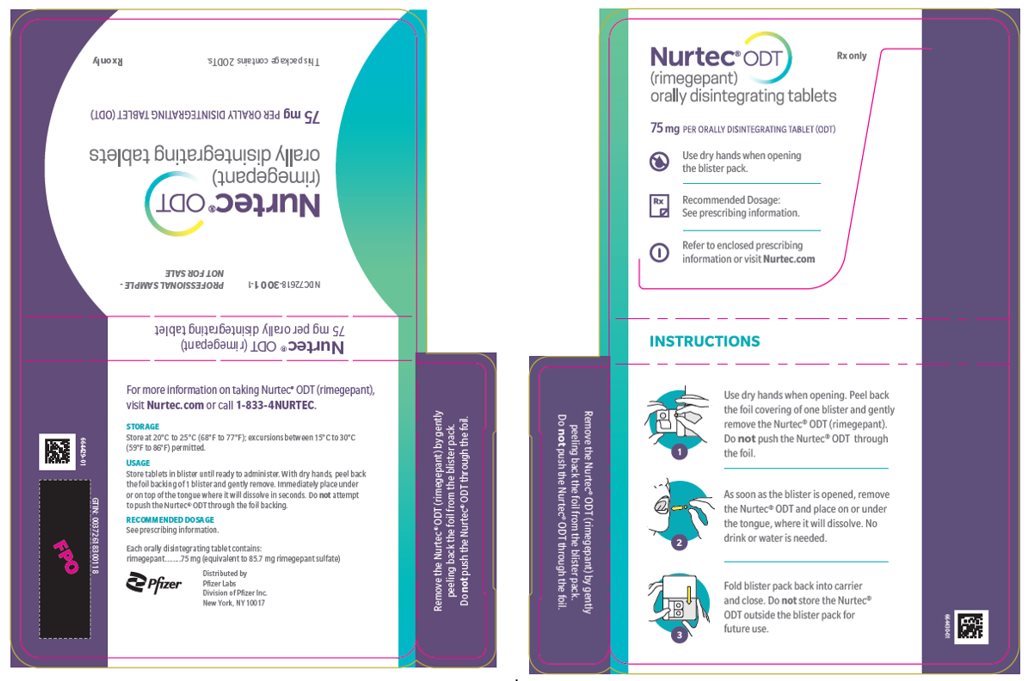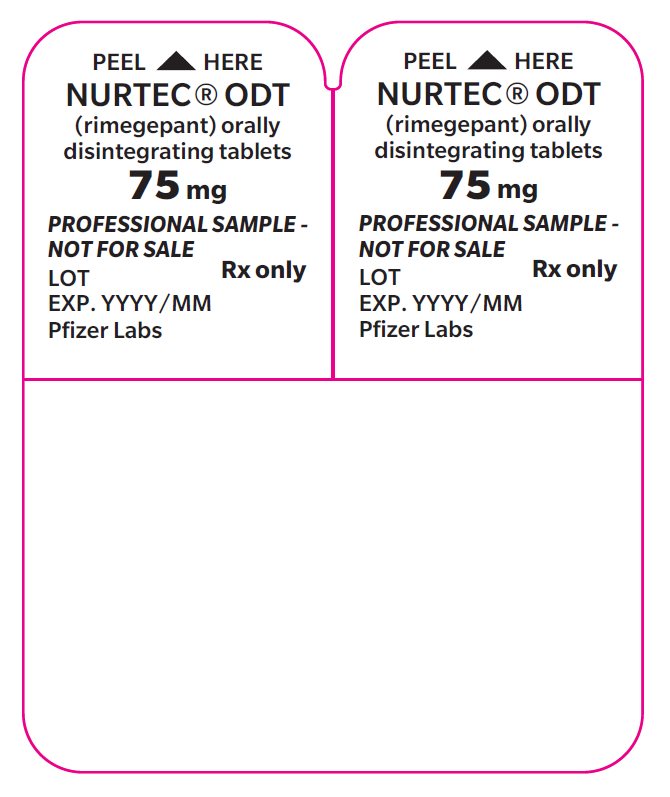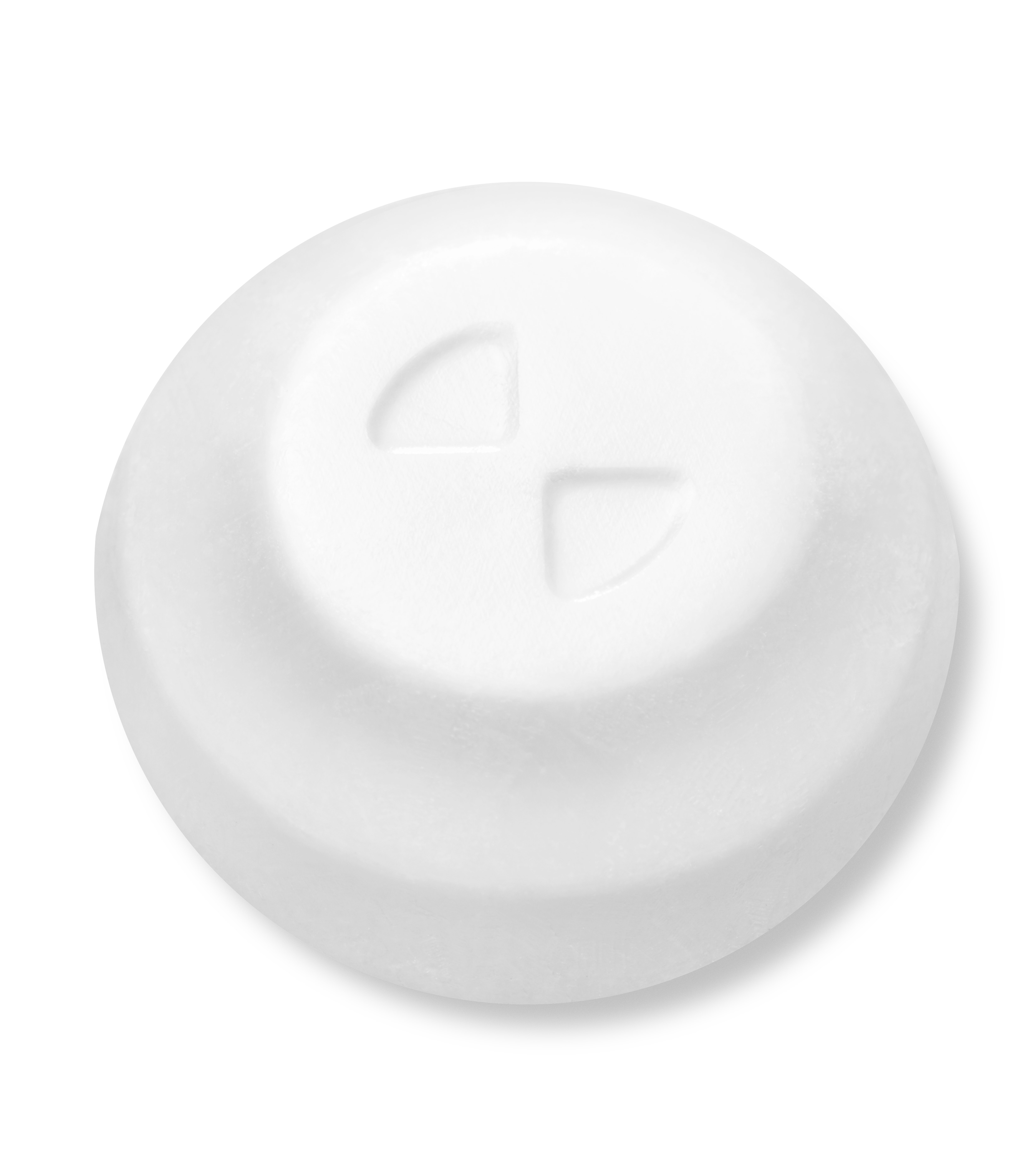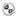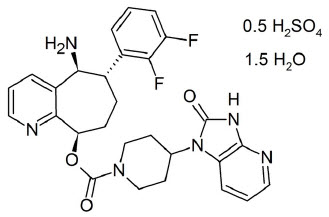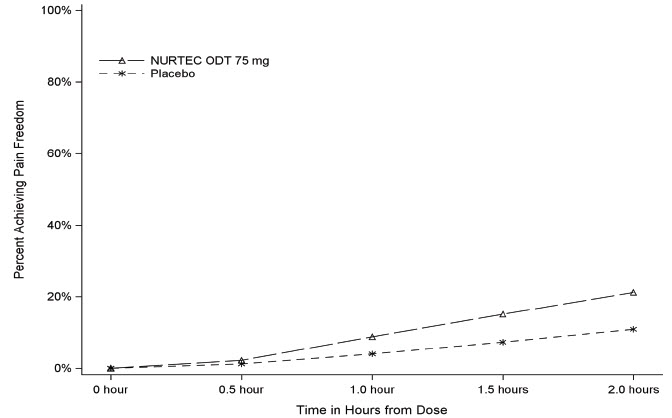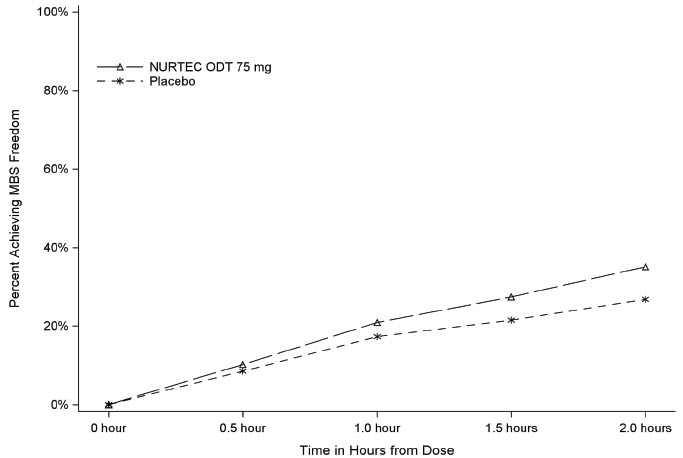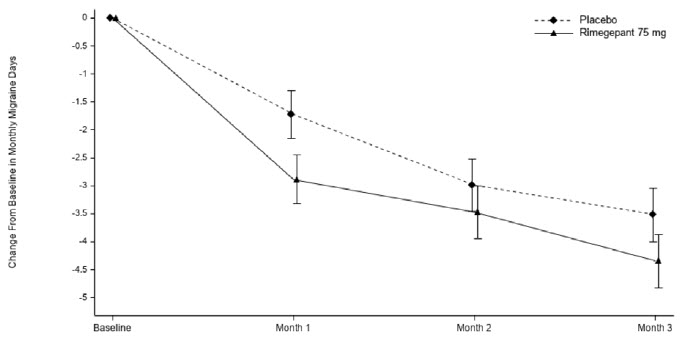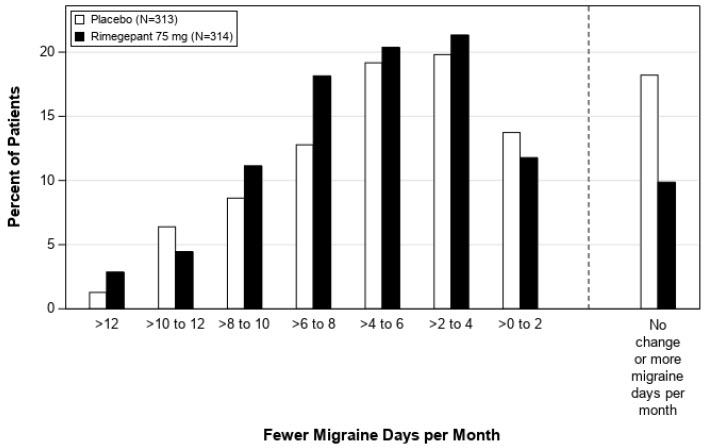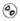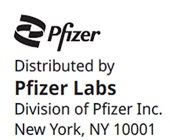 DRUG LABEL: NURTEC ODT
NDC: 72618-3000 | Form: TABLET, ORALLY DISINTEGRATING
Manufacturer: Pfizer Laboratories Div Pfizer Inc
Category: prescription | Type: HUMAN PRESCRIPTION DRUG LABEL
Date: 20260114

ACTIVE INGREDIENTS: RIMEGEPANT SULFATE 75 mg/1 1
INACTIVE INGREDIENTS: SUCRALOSE; EUCALYPTOL; MARINE NON-GELLING GELATIN, HIGH MW; LIMONENE, (+)-; BENZYL ALCOHOL; MENTHYL ACETATE, (+/-)-; VANILLIN; MENTHOL, UNSPECIFIED FORM; MENTHONE, (+)-; MANNITOL

HIGHLIGHTS OF PRESCRIBING INFORMATION

These highlights do not include all the information needed to use NURTEC® ODT safely and effectively. See full prescribing information for NURTEC ODT.
NURTEC ODT (rimegepant) orally disintegrating tablets, for sublingual or oral use
Initial U.S. Approval: 2020

RECENT MAJOR CHANGES

Contraindications (4) | 08/2025
Warnings and Precautions (5.1) | 08/2025
Warnings and Precautions (5.2, 5.3) | 3/2025

1 INDICATIONS AND USAGE

NURTEC ODT is a calcitonin gene-related peptide receptor antagonist indicated for the:

- acute treatment of migraine with or without aura in adults (1.1)
- preventive treatment of episodic migraine in adults (1.2)

2 DOSAGE AND ADMINISTRATION

- Recommended dosage for acute treatment of migraine: 75 mg taken orally, as needed. (2.1)
- The safety of using more than 18 doses in a 30-day period has not been established. (2.1)
- Recommended dosage for preventive treatment of episodic migraine: 75 mg taken orally every other day. (2.2)
- The maximum dose in a 24-hour period is 75 mg. (2.1)

3 DOSAGE FORMS AND STRENGTHS

NURTEC ODT orally disintegrating tablets: 75 mg (3)

4 CONTRAINDICATIONS

Patients with a history of hypersensitivity reaction to rimegepant, NURTEC ODT, or to any of its components. (4)

5 WARNINGS AND PRECAUTIONS

- Hypersensitivity Reactions: If a serious hypersensitivity reaction occurs, discontinue NURTEC ODT and initiate appropriate therapy. Severe hypersensitivity reactions have included anaphylaxis, dyspnea, and rash, and can occur days after administration. (5.1)
- Hypertension: New-onset or worsening of pre-existing hypertension may occur. (5.2)
- Raynaud’s Phenomenon: New-onset or worsening of pre-existing Raynaud’s phenomenon may occur. (5.3)

6 ADVERSE REACTIONS

Acute treatment of migraine: the adverse reaction reported in ≥ 1% of patients treated with NURTEC ODT is nausea. (6.1)
  Preventive treatment of episodic migraine: adverse reactions reported in ≥ 2% for rimegepant and ≥ 1% higher than placebo are nausea and abdominal pain/dyspepsia. (6.1)

To report SUSPECTED ADVERSE REACTIONS, contact Pfizer Inc. at 1-800-438-1985 or FDA at 1-800-FDA-1088 or www.fda.gov/medwatch.

7 DRUG INTERACTIONS

- Strong CYP3A4 Inhibitors: Avoid concomitant administration. (7.1)
- Moderate CYP3A4 Inhibitors: Avoid another dose within 48 hours when administered with a moderate CYP3A4 inhibitor. (7.1)
- Strong and Moderate CYP3A Inducers: Avoid concomitant administration. (7.2)
- Potent Inhibitors of P-gp: Avoid another dose of NURTEC ODT within 48 hours when administered with a potent P-gp inhibitor. (7.3)

8 USE IN SPECIFIC POPULATIONS

- Exposures were significantly higher in subjects with severe hepatic impairment. Avoid use in patients with severe hepatic impairment (Child-Pugh C). (8.6)

FULL PRESCRIBING INFORMATION

1 INDICATIONS AND USAGE

1.1 Acute Treatment of Migraine

NURTEC ODT is indicated for the acute treatment of migraine with or without aura in adults.

1.2 Preventive Treatment of Episodic Migraine

NURTEC ODT is indicated for the preventive treatment of episodic migraine in adults.

2 DOSAGE AND ADMINISTRATION

2.1 Recommended Dosing for Acute Treatment of Migraine

The recommended dose of NURTEC ODT is 75 mg taken orally, as needed.

The maximum dose in a 24-hour period is 75 mg. The safety of using more than 18 doses in a 30-day period has not been established.

2.2 Recommended Dosing for Preventive Treatment of Episodic Migraine

The recommended dosage of NURTEC ODT is 75 mg taken orally every other day.

2.3 Administration Information

Instruct the patient on the following administration instructions:

- Use dry hands when opening the blister pack.
- Peel back the foil covering of one blister and gently remove the orally disintegrating tablet (ODT). Do not push the ODT through the foil.
- As soon as the blister is opened, remove the ODT and place on the tongue; alternatively, the ODT may be placed under the tongue.
- The ODT will disintegrate in saliva so that it can be swallowed without additional liquid.
- Take the ODT immediately after opening the blister pack. Do not store the ODT outside the blister pack for future use.

2.4 Concomitant Administration with Strong or Moderate CYP3A4 Inhibitors

Avoid concomitant administration of NURTEC ODT with strong inhibitors of CYP3A4. Avoid another dose of NURTEC ODT within 48 hours when it is concomitantly administered with moderate inhibitors of CYP3A4 [see Drug Interactions (7.1), Clinical Pharmacology (12.3)].

2.5 Concomitant Administration with Strong or Moderate CYP3A Inducers

Avoid concomitant administration of NURTEC ODT with strong or moderate inducers of CYP3A, which may lead to loss of efficacy of NURTEC ODT [see Drug Interactions (7.2), Clinical Pharmacology (12.3)].

2.6 Concomitant Administration with Potent Inhibitors of P-gp

Avoid another dose of NURTEC ODT within 48 hours when it is concomitantly administered with potent inhibitors of P-gp [see Drug Interactions (7.3), Clinical Pharmacology (12.3)].

3 DOSAGE FORMS AND STRENGTHS

Orally disintegrating tablets: white to off-white, circular, and debossed with the symbol , each containing 75 mg of rimegepant.

4 CONTRAINDICATIONS

NURTEC ODT is contraindicated in patients with a history of hypersensitivity reaction to rimegepant, NURTEC ODT, or any of its components. Reactions have included anaphylaxis and delayed serious hypersensitivity [see Warnings and Precautions (5.1)].

5 WARNINGS AND PRECAUTIONS

5.1 Hypersensitivity Reactions

Serious hypersensitivity reactions, including anaphylaxis, dyspnea, and rash, have occurred in patients treated with NURTEC ODT. Hypersensitivity reactions can occur days after administration, and delayed serious hypersensitivity has occurred. If a hypersensitivity reaction occurs, discontinue NURTEC ODT and initiate appropriate therapy [see Contraindications (4) and Adverse Reactions (6.1, 6.2)].

5.2 Hypertension

Development of hypertension and worsening of pre-existing hypertension have been reported following the use of CGRP antagonists, including NURTEC ODT, in the postmarketing setting.

Some of the patients who developed new-onset hypertension had risk factors for hypertension. There were cases requiring initiation of pharmacological treatment for hypertension and, in some cases, hospitalization. Hypertension may occur at any time during treatment, but was most frequently reported within 7 days of therapy initiation. NURTEC ODT was discontinued in many of the reported cases.

Monitor patients treated with NURTEC ODT for new-onset hypertension or worsening of pre-existing hypertension, and consider whether discontinuation of NURTEC ODT is warranted if evaluation fails to establish an alternative etiology or blood pressure is inadequately controlled.

5.3 Raynaud’s Phenomenon

Development of Raynaud’s phenomenon and recurrence or worsening of pre-existing Raynaud’s phenomenon have been reported in the postmarketing setting following the use of CGRP antagonists, including NURTEC ODT.

In reported cases with small molecule CGRP antagonists, symptom onset occurred a median of 1.5 days following dosing. Many of the cases reported serious outcomes, including hospitalizations and disability, generally related to debilitating pain. In most reported cases, discontinuation of the CGRP antagonist resulted in resolution of symptoms.

NURTEC ODT should be discontinued if signs or symptoms of Raynaud’s phenomenon develop, and patients should be evaluated by a healthcare provider if symptoms do not resolve. Patients with a history of Raynaud’s phenomenon should be monitored for, and informed about the possibility of, worsening or recurrence of signs and symptoms.

6 ADVERSE REACTIONS

The following clinically significant adverse reactions are discussed in greater detail in other sections of the labeling:

- Hypersensitivity Reactions [see Warnings and Precautions (5.1)]
- Hypertension [see Warnings and Precautions (5.2)]
- Raynaud’s Phenomenon [see Warnings and Precautions (5.3)]

6.1 Clinical Trials Experience

Because clinical trials are conducted under widely varying conditions, adverse reaction rates observed in the clinical trials of a drug cannot be directly compared to rates in the clinical trials of another drug and may not reflect the rates observed in clinical practice.

Acute Treatment of Migraine

The safety of NURTEC ODT for the acute treatment of migraine in adults has been evaluated in a randomized, double-blind, placebo-controlled trial (Study 1) in 682 patients with migraine who received one 75 mg dose of NURTEC ODT [see Clinical Studies (14)]. Approximately 85% were female, 74% were White, 21% were Black, and 17% were Hispanic or Latino. The mean age at study entry was 40 years (range 18-75 years of age).

Long-term safety was assessed in an open-label extension study using a different oral dosage form of rimegepant. That study evaluated 1,798 patients, dosing intermittently for up to one year, including 1,131 patients who were exposed to rimegepant 75 mg for at least 6 months, and 863 who were exposed for at least one year, all of whom treated an average of at least two migraine attacks per month.

The most common adverse reaction in Study 1 was nausea (2% in patients who received NURTEC ODT compared to 0.4% of patients who received placebo).

Hypersensitivity, including dyspnea and severe rash, occurred in less than 1% of patients treated with NURTEC ODT [see Contraindications (4) and Warnings and Precautions (5.1)].

Preventive Treatment of Episodic Migraine

The safety of NURTEC ODT for the preventive treatment of episodic migraine in adults has been established in a randomized, double-blind, placebo-controlled trial with an open-label extension (Study 2) using a different oral dosage form of rimegepant [see Clinical Studies (14)]. In the 12-week, double-blind treatment period, 370 patients with migraine received one 75 mg dose of rimegepant every other day. Approximately 81% were female, 80% were White, 17% were Black, and 28% were Hispanic or Latino. The mean age at study entry was 41 years (range 18-74 years of age). Long-term safety was assessed in an open-label extension study that included 603 patients who were treated for up to one year. Overall, 527 patients were exposed to rimegepant 75 mg for at least 6 months, and 311 were exposed for at least one year.

The most common adverse reactions (occurring in at least 2% of rimegepant-treated patients and at a frequency of at least 1% higher than placebo) in Study 2 were nausea (2.7% in patients who received rimegepant compared with 0.8% of patients who received placebo) and abdominal pain/dyspepsia (2.4% in patients who received rimegepant compared with 0.8% of patients who received placebo).

6.2 Postmarketing Experience

The following adverse reactions have been identified during postapproval use of NURTEC ODT. Because these reactions are reported voluntarily from a population of uncertain size, it is not always possible to reliably estimate their frequency or establish a causal relationship to drug exposure.

Immune System Disorders: Hypersensitivity (e.g., anaphylaxis) [see Contraindications (4) and Warnings and Precautions (5.1)]

Vascular Disorders: Hypertension [see Warnings and Precautions (5.2)], Raynaud’s phenomenon [see Warnings and Precautions (5.3)]

7 DRUG INTERACTIONS

7.1 CYP3A4 Inhibitors

Concomitant administration of NURTEC ODT with strong inhibitors of CYP3A4 results in a significant increase in rimegepant exposure. Avoid concomitant administration of NURTEC ODT with strong inhibitors of CYP3A4 [see Clinical Pharmacology (12.3)].

Concomitant administration of NURTEC ODT with moderate inhibitors of CYP3A4 may result in increased exposure of rimegepant. Avoid another dose of NURTEC ODT within 48 hours when it is concomitantly administered with moderate inhibitors of CYP3A4 [see Clinical Pharmacology (12.3)].

7.2 CYP3A Inducers

Concomitant administration of NURTEC ODT with strong or moderate inducers of CYP3A can result in a significant reduction in rimegepant exposure, which may lead to loss of efficacy of NURTEC ODT. Avoid concomitant administration of NURTEC ODT with strong or moderate inducers of CYP3A [see Clinical Pharmacology (12.3)].

7.3 P-gp Inhibitors

Concomitant administration of NURTEC ODT with potent inhibitors of P-gp (e.g., amiodarone, cyclosporine, lapatinib, quinidine, ranolazine) may result in increased exposure of rimegepant. Avoid another dose of NURTEC ODT within 48 hours when it is concomitantly administered with potent inhibitors of P-gp [see Clinical Pharmacology (12.3)].

8 USE IN SPECIFIC POPULATIONS

8.1 Pregnancy

Pregnancy Exposure Registry

There is a pregnancy exposure registry that monitors pregnancy outcomes in women exposed to NURTEC ODT during pregnancy. For more information, healthcare providers or patients are encouraged to contact: 1-877-366-0324, email nurtecpregnancyregistry@ppd.com, or visit nurtecpregnancyregistry.com.

Risk Summary

There are no adequate data on the developmental risk associated with the use of NURTEC ODT in pregnant women. In animal studies, oral administration of rimegepant during organogenesis resulted in adverse effects on development in rats (decreased fetal body weight and increased incidence of skeletal variations) at exposures greater than those used clinically and which were associated with maternal toxicity (see Data).

In the U.S. general population, the estimated background risk of major birth defects and miscarriage in clinically recognized pregnancies is 2 to 4% and 15 to 20%, respectively. The estimated rate of major birth defects (2.2 to 2.9%) and miscarriage (17%) among deliveries to women with migraine are similar to rates reported in women without migraine.

Clinical Considerations

Disease-Associated Maternal and/or Embryo/Fetal Risk

Published data have suggested that women with migraine may be at increased risk of preeclampsia and gestational hypertension during pregnancy.

Data

Animal Data

Oral administration of rimegepant (0, 10, 60, or 300 mg/kg/day) to pregnant rats during the period of organogenesis resulted in decreased fetal body weight and an increased incidence of fetal skeletal variations at the highest dose tested (300 mg/kg/day), which was associated with maternal toxicity. Plasma exposures (AUC) at the no-effect dose (60 mg/kg/day) for adverse effects on embryofetal development were approximately 45 times that in humans at the maximum recommended human dose (MRHD) of 75 mg/day.

Oral administration of rimegepant (0, 10, 25, or 50 mg/kg/day) to pregnant rabbits during the period of organogenesis resulted in no adverse effects on embryofetal development. The highest dose tested (50 mg/kg/day) was associated with plasma exposures (AUC) approximately 10 times that in humans at the MRHD.

Oral administration of rimegepant (0, 10, 25, or 60 mg/kg/day) to rats throughout gestation and lactation resulted in no effects on pre- or postnatal development. The highest dose tested (60 mg/kg/day) was associated with plasma exposures (AUC) approximately 24 times that in humans at the MRHD.

8.2 Lactation

Risk Summary

A lactation study was conducted, and the results have established a relative infant dose of less than 1% of the maternal weight-adjusted dose and the milk-to-plasma ratio of 0.20 (see Data). These data support that transfer of rimegepant into breastmilk is low. There are no data on the effects of rimegepant on a breastfed infant or on milk production.

The developmental and health benefits of breastfeeding should be considered along with the mother's clinical need for NURTEC ODT and any potential adverse effects on the breastfed infant from NURTEC ODT or from the underlying maternal condition.

Data

A study was conducted in twelve healthy adult lactating women who were between 2 weeks and 6 months postpartum and were administered a single oral dose of rimegepant 75 mg. The relative infant dose was < 1%. The average milk to plasma ratio was 0.20.

8.4 Pediatric Use

Safety and effectiveness in pediatric patients have not been established.

8.5 Geriatric Use

In pharmacokinetic studies, no clinically significant pharmacokinetic differences were observed between elderly and younger subjects. Clinical studies of NURTEC ODT did not include sufficient numbers of patients aged 65 and over to determine whether they respond differently from younger patients.

8.6 Hepatic Impairment

No dosage adjustment of NURTEC ODT is required in patients with mild (Child-Pugh A) or moderate (Child-Pugh B) hepatic impairment. Plasma concentrations of rimegepant were significantly higher in subjects with severe (Child-Pugh C) hepatic impairment. Avoid use of NURTEC ODT in patients with severe hepatic impairment [see Clinical Pharmacology (12.3)].

8.7 Renal Impairment

No dosage adjustment of NURTEC ODT is required in patients with mild, moderate, or severe renal impairment. NURTEC ODT has not been studied in patients with end-stage renal disease and in patients on dialysis. Avoid use of NURTEC ODT in patients with end-stage renal disease (CLcr < 15 mL/min) [see Clinical Pharmacology (12.3)].

10 OVERDOSAGE

There is limited clinical experience with NURTEC ODT overdosage. Treatment of an overdose of NURTEC ODT should consist of general supportive measures including monitoring of vital signs and observation of the clinical status of the patient. No specific antidote for the treatment of rimegepant overdose is available. Rimegepant is unlikely to be significantly removed by dialysis because of high serum protein binding [see Clinical Pharmacology (12.3)].

11 DESCRIPTION

NURTEC ODT contains rimegepant sulfate, a calcitonin gene-related peptide receptor antagonist. Rimegepant sulfate is described chemically as (5S,6S,9R)-5-amino-6-(2,3-difluorophenyl)-6,7,8,9-tetrahydro-5H-cyclohepta[b]pyridin-9-yl 4-(2-oxo-2,3-dihydro-1H-imidazo[4,5-b]pyridin-1-yl)-1-piperidinecarboxylate hemisulfate sesquihydrate and its structural formula is:

Its empirical formula is C28H28F2N6O3 0.5 H2SO4 1.5 H2O, representing a molecular weight of 610.63. Rimegepant free base has a molecular weight of 534.56. Rimegepant sulfate is a white to off-white, crystalline solid that is slightly soluble in water.

NURTEC ODT (orally disintegrating tablets) is for sublingual or oral use and contains 85.7 mg rimegepant sulfate, equivalent to 75 mg rimegepant free base, and the following inactive ingredients: benzyl alcohol, eucalyptol, gelatin, limonene, mannitol, menthol, menthone, menthyl acetate, sucralose, and vanillin.

12 CLINICAL PHARMACOLOGY

12.1 Mechanism of Action

Rimegepant is a calcitonin gene-related peptide receptor antagonist.

12.2 Pharmacodynamics

The relationship between pharmacodynamic activity and the mechanism(s) by which rimegepant exerts its clinical effects is unknown.

No clinically relevant differences in resting blood pressure were observed when rimegepant was concomitantly administered with sumatriptan (12 mg subcutaneous, given as two 6 mg doses separated by one hour) compared with sumatriptan alone to healthy volunteers.

Cardiac Electrophysiology

At a single dose 4 times the recommended dose, rimegepant does not prolong the QT interval to any clinically relevant extent.

12.3 Pharmacokinetics

Absorption

Following oral administration of NURTEC ODT, rimegepant is absorbed with the maximum concentration at 1.5 hours. The absolute oral bioavailability of rimegepant is approximately 64%.

Effects of Food

Following administration of NURTEC ODT under fed conditions with a high-fat or low-fat meal, Tmax was delayed by approximately 1 to 1.5 hours. A high-fat meal reduced Cmax by 42 to 53% and AUC by 32 to 38%. A low-fat meal reduced Cmax by 36% and AUC by 28%. NURTEC ODT was administered without regard to food in clinical safety and efficacy studies. The impact of the reduction in rimegepant exposure because of administration with food on its efficacy is unknown.

Distribution

The steady state volume of distribution of rimegepant is 120 L. Plasma protein binding of rimegepant is approximately 96%.

Elimination

Metabolism

Rimegepant is primarily metabolized by CYP3A4 and to a lesser extent by CYP2C9.

Rimegepant is the primary form (~77%) with no major metabolites (i.e., > 10%) detected in plasma.

Excretion

The elimination half-life of rimegepant is approximately 11 hours in healthy subjects. Following oral administration of [^14C]-rimegepant to healthy male subjects, 78% of the total radioactivity was recovered in feces and 24% in urine. Unchanged rimegepant is the major single component in excreted feces (42%) and urine (51%).

Specific Populations

Renal Impairment

In a dedicated clinical study comparing the pharmacokinetics of rimegepant in subjects with mild (estimated creatinine clearance [CLcr] 60-89 mL/min), moderate (CLcr 30-59 mL/min), and severe (CLcr 15-29 mL/min) renal impairment to that with normal subjects (healthy matched control), the exposure of rimegepant following single 75 mg dose was approximately 40% higher in subjects with moderate renal impairment. However, there was no clinically meaningful difference in the exposure of rimegepant in subjects with severe renal impairment compared to subjects with normal renal function (CLcr >= 90 mL/min). NURTEC ODT has not been studied in patients with end-stage renal disease (CLcr < 15 mL/min) [see Use in Specific Populations (8.7)].

Hepatic Impairment

In a dedicated clinical study comparing the pharmacokinetics of rimegepant in subjects with mild, moderate, and severe hepatic impairment to that with normal subjects (healthy matched control), the exposure of rimegepant (Cmax and AUC) following single 75 mg dose was approximately 2-fold higher in subjects with severe impairment (Child-Pugh class C). There were no clinically meaningful differences in the exposure of rimegepant in subjects with mild (Child-Pugh class A) and moderate hepatic impairment (Child-Pugh class B) compared to subjects with normal hepatic function [see Use in Specific Populations (8.6)].

Other Specific Populations

No clinically significant differences in the pharmacokinetics of rimegepant were observed based on age, sex, race/ethnicity, body weight, or CYP2C9 genotype [see Clinical Pharmacology (12.5)].

Drug Interaction Studies

In Vitro Studies

- Enzymes

Rimegepant is a substrate of CYP3A4 and CYP2C9 (see In Vivo Studies). Rimegepant is not an inhibitor of CYP1A2, 2B6, 2C9, 2C19, 2D6, or UGT1A1 at clinically relevant concentrations. However, rimegepant is a weak inhibitor of CYP3A4 with time-dependent inhibition. Rimegepant is not an inducer of CYP1A2, CYP2B6, or CYP3A4 at clinically relevant concentrations.

- Transporters

Rimegepant is a substrate of P-gp and BCRP (see In Vivo Studies).

Rimegepant is not a substrate of OATP1B1 or OATP1B3. Considering its low renal clearance, rimegepant was not evaluated as a substrate of the OAT1, OAT3, OCT2, MATE1, or MATE2-K.

Rimegepant is not an inhibitor of P-gp, BCRP, OAT1, or MATE2-K at clinically relevant concentrations. It is a weak inhibitor of OATP1B1 and OAT3. Rimegepant is an inhibitor of OATP1B3, OCT2, and MATE1. In a dedicated interaction study, concomitant administration of 75 mg rimegepant at steady state with metformin, a MATE1 transporter substrate, at steady state resulted in no clinically significant impact on either metformin pharmacokinetics or on glucose utilization. No clinical drug interactions are expected for NURTEC ODT with OATP1B3 or OCT2, at clinically relevant concentrations.

In Vivo Studies

CYP3A4 Inhibitors

In a dedicated drug interaction study, concomitant administration of 75 mg rimegepant (single dose) with itraconazole, a strong CYP3A4 inhibitor, at steady state resulted in increased exposures of rimegepant (AUC by 4-fold and Cmax by ~1.5-fold) [see Drug Interactions (7.1)]. No dedicated drug interaction study was conducted to assess the effect of concomitant administration of a weak inhibitor of CYP3A4 on the pharmacokinetics of rimegepant. The concomitant administration of rimegepant with a moderate inhibitor of CYP3A4 may increase rimegepant exposures (AUC) by less than 2-fold [see Drug Interactions (7.1)]. Concomitant administration of rimegepant with a weak inhibitor of CYP3A4 is not expected to have a clinically significant impact on rimegepant exposures.

CYP3A Inducers

In a dedicated drug interaction study, concomitant administration of 75 mg rimegepant (single dose) with rifampin, a strong CYP3A4 inducer, at steady state resulted in decreased exposures of rimegepant (AUC by 80% and Cmax by 64%), which may lead to loss of efficacy [see Drug Interactions (7.2)]. No dedicated drug interaction study was conducted to assess the effect of concomitant administration of a moderate or weak inducer of CYP3A4 on the pharmacokinetics of rimegepant. Since rimegepant is a moderately sensitive substrate for CYP3A4, drugs that are moderate inducers of CYP3A4 can also cause significant reduction in rimegepant exposure resulting in loss of efficacy [see Drug Interactions (7.2)]. Clinically significant interaction is not expected with concomitant administration of weak inducers of CYP3A4 and rimegepant.

CYP2C9 Inhibitors

In a dedicated drug interaction study, concomitant administration of 75 mg rimegepant (single dose) with fluconazole, a combined moderate CYP3A4 and CYP2C9 inhibitor, resulted in increased exposures of rimegepant (AUC by 1.8-fold) with no relevant effect on Cmax. Rimegepant is primarily metabolized by CYP3A4 and to a lesser extent by CYP2C9. Increase in the exposure of rimegepant can be attributed to combined inhibition of CYP2C9 and CYP3A4 with fluconazole administration suggesting a minor contribution from CYP2C9. Thus, CYP2C9 inhibition alone is not expected to significantly affect rimegepant exposures.

P-gp and BCRP Inhibitors

In a dedicated drug interaction study, concomitant administration of NURTEC ODT with cyclosporine (a potent P-gp and BCRP inhibitor) and with quinidine (a potent P-gp inhibitor) resulted in an increase of similar magnitude in rimegepant exposure (AUC and Cmax by 1.6 and 1.4 fold with cyclosporine, and by 1.6 and 1.7 fold with quinidine, respectively) [see Drug Interactions (7.3)]. Therefore, concomitant administration of NURTEC ODT with BCRP inhibitors is not expected to have a clinically significant impact on rimegepant exposures.

Other Drugs: No significant pharmacokinetic interactions were observed when rimegepant was concomitantly administered with oral contraceptives (norelgestromin, ethinyl estradiol), midazolam (a sensitive CYP3A4 substrate), metformin (a MATE1 substrate), or sumatriptan [see Clinical Pharmacology (12.2)].

12.5 Pharmacogenomics

CYP2C9 activity is reduced in individuals with genetic variants such as the CYP2C9*2 and CYP2C9*3 alleles. Rimegepant Cmax and AUC0-inf were similar in CYP2C9 intermediate metabolizers (i.e., *1/*2, *2/*2, *1/*3, n=43) as compared to normal metabolizers (i.e., *1/*1, N=72). Adequate PK data are not available from CYP2C9 poor metabolizers (i.e., *2/*3). Since the contribution of CYP2C9 to rimegepant metabolism is considered minor, CYP2C9 polymorphism is not expected to significantly affect its exposure.

13 NONCLINICAL TOXICOLOGY

13.1 Carcinogenesis, Mutagenesis, Impairment of Fertility

Carcinogenesis

Oral administration of rimegepant to Tg.rasH2 mice (0, 10, 100, or 300 mg/kg/day) for 26 weeks and to rats (0, 5, 20, or 45 mg/kg/day) for 91-100 weeks resulted in no evidence of drug-induced tumors in either species. In rats, the plasma exposure (AUC) at the highest dose tested (45 mg/kg/day) was approximately 30 times that at the maximum recommended human dose (MRHD) of 75 mg/day.

Mutagenesis

Rimegepant was negative in in vitro (bacterial reverse-mutation, chromosomal aberration in Chinese hamster ovary cells) and in vivo (rat micronucleus) assays.

Impairment of Fertility

Oral administration of rimegepant (0, 30, 60, or 150 mg/kg/day) to male and female rats prior to and during mating and continuing in females to gestation day (GD) 7 resulted in reduced fertility at the highest dose tested. In a second fertility study testing lower doses (0, 5, 15, or 25 mg/kg/day), no adverse effects on fertility, uterine histopathology, or early embryonic development were observed. The no-effect dose for impairment of fertility and early embryonic development in rats (60 mg/kg/day) was associated with plasma drug exposures (AUC) approximately 30 times that in humans at the MRHD.

14 CLINICAL STUDIES

14.1 Acute Treatment of Migraine

The efficacy of NURTEC ODT for the acute treatment of migraine with and without aura in adults was demonstrated in a randomized, double-blind, placebo-controlled trial: Study 1 (NCT03461757). Patients in the study were randomized to receive 75 mg of NURTEC ODT (N=732) or placebo (N=734). Patients were instructed to treat a migraine of moderate to severe headache pain intensity. Rescue medication (i.e., NSAIDs, acetaminophen, and/or an antiemetic) was allowed 2 hours after the initial treatment. Other forms of rescue medication such as triptans were not allowed within 48 hours of initial treatment. Approximately 14% of patients were taking preventive medications for migraine at baseline. None of the patients in Study 1 were on concomitant preventive medication that act on the CGRP pathway.

The primary efficacy analyses were conducted in patients who treated a migraine with moderate to severe pain. NURTEC ODT 75 mg demonstrated an effect on pain freedom and most bothersome symptom (MBS) freedom at two hours after dosing, compared to placebo. Pain freedom was defined as a reduction of moderate or severe headache pain to no headache pain, and MBS freedom was defined as the absence of the self-identified MBS (i.e., photophobia, phonophobia, or nausea). Among patients who selected an MBS, the most commonly selected symptom was photophobia (54%), followed by nausea (28%), and phonophobia (15%).

In Study 1, the percentage of patients achieving headache pain freedom and MBS freedom two hours after a single dose was statistically significantly greater in patients who received NURTEC ODT compared to those who received placebo (Table 1).

Table 1: Efficacy Endpoints for the Acute Treatment of Migraine in Study 1
 | Study 1
 | NURTEC ODT 75 mg | Placebo
Pain Free at 2 hours
n/N [n=number of responders/N=number of patients in that treatment group] | 142/669 | 74/682
% Responders | 21.2 | 10.9
Difference from placebo (%) | 10.3
p-value |  | <0.001
MBS Free at 2 hours
n/N | 235/669 | 183/682
% Responders | 35.1 | 26.8
Difference from placebo (%) | 8.3
p-value |  | 0.001

Figure 1 presents the percentage of patients achieving migraine pain freedom within 2 hours following treatment in Study 1.

Figure 1: Percentage of Patients Achieving Pain Freedom within 2 Hours in Study 1

Figure 2 presents the percentage of patients achieving MBS freedom within 2 hours in Study 1.

Figure 2: Percentage of Patients Achieving MBS Freedom within 2 Hours in Study 1

In Study 1, statistically significant effects of NURTEC ODT compared to placebo were demonstrated for the additional efficacy endpoints of pain relief at 2 hours, sustained pain freedom 2-48 hours, use of rescue medication within 24 hours, and the percentage of patients reporting normal function at two hours after dosing (Table 2). Pain relief was defined as a reduction in migraine pain from moderate or severe severity to mild or none. The measurement of the percentage of patients reporting normal function at two hours after dosing was derived from a single item questionnaire, asking patients to select one response on a 4-point scale; normal function, mild impairment, severe impairment, or required bedrest.

Table 2: Additional Acute Treatment of Migraine Efficacy Endpoints in Study 1
 | Study 1
 | NURTEC ODT 75 mg | Placebo
Pain Relief at 2 hours
n/N [n=number of responders/N=number of patients in that treatment group] | 397/669 | 295/682
% Responders | 59.3 | 43.3
Difference from placebo | 16.1
p-value |  | <0.001
Sustained Pain Freedom 2-48 hours
n/N | 90/669 | 37/682
% Responders | 13.5 | 5.4
Difference from placebo | 8.0
p-value |  | <0.001
Use of Rescue Medication within 24 hours [This analysis includes only the use of NSAIDs, acetaminophen, or antiemetics, within 24 hours post-dose; the use of triptans, or other acute migraine medication, was not allowed.]
n/N | 95/669 | 199/682
% Responders | 14.2 | 29.2
Difference from placebo | -15.0
p-value |  | <0.001
Percentage of Patients Reporting Normal Function at 2 hours
n/N | 255/669 | 176/682
Responders | 38.1 | 25.8
Difference from placebo | 12.3
p-value |  | <0.001

The incidence of photophobia and phonophobia was reduced following administration of NURTEC ODT 75 mg as compared to placebo.

14.2 Preventive Treatment of Episodic Migraine

The efficacy of NURTEC ODT for the preventive treatment of episodic migraine in adults was demonstrated in one randomized, double-blind, placebo-controlled trial of a different oral dosage form of rimegepant (Study 2; NCT03732638).

Study 2 enrolled adult patients with at least a 1-year history of migraine (with or without aura). Patients experienced an average of 10.9 headache days during the 28-day observational period, which included an average of 10.2 migraine days, prior to randomization into the trial. Patients were randomized to receive every other day dosing of rimegepant 75 mg (N=373) or placebo (N=374) for 12 weeks. Patients were allowed to use acute headache treatments (i.e., triptans, NSAIDs, acetaminophen, antiemetics, muscle relaxants, and aspirin) as needed. Approximately 10% of patients were taking one preventive medication for migraine at baseline. The use of a concomitant medication that acts on the CGRP pathway was not permitted for either the acute or preventive treatment of migraine.

The study excluded patients with myocardial infarction, acute coronary syndrome, percutaneous coronary intervention, cardiac surgery, stroke, or transient ischemic attack within six months of screening.

The primary efficacy endpoint for Study 2 was the change from baseline in the mean number of monthly migraine days (MMDs) during Weeks 9 through 12 of the double-blind treatment phase.

The percentage of patients who achieved at least a 50% reduction from baseline in moderate to severe MMDs during Weeks 9 through 12 of the double-blind treatment phase compared to placebo was also evaluated. Rimegepant 75 mg dosed every other day demonstrated statistically significant improvements for these efficacy endpoints compared to placebo, as summarized in Table 3.

Table 3: Efficacy Endpoints for the Preventive Treatment of Episodic Migraine in Study 2
 | Rimegepant 75 mg Every Other Day | Placebo Every Other Day
Monthly Migraine Days (MMD), Weeks 9-12 | N=348 | N=347
Change from baseline | -4.3 | -3.5
Change from placebo | -0.8
p-value | 0.010
≥ 50% Responders (Moderate to Severe MMDs), Weeks 9-12 | N=348 | N=347
% Responders | 49.1 | 41.5
Difference from placebo | 7.6
p-value | 0.044

Figure 3: Change from Baseline in Monthly Migraine Days in Study 2a

aLeast-square means and 95% confidence intervals are presented.

Figure 4: Distribution of Change from Baseline in Mean Monthly Migraine Days at Month 3 by Treatment Group in Study 2a

aFigure excludes patients with missing data.

16 HOW SUPPLIED/STORAGE AND HANDLING

16.1 How Supplied

NURTEC ODT 75 mg orally disintegrating tablets are white to off-white, circular, debossed with the symbol , and supplied in cartons containing a blister pack of 8 orally disintegrating tablets. Each ODT contains 75 mg rimegepant.

NDC: 72618-3000-2

16.2 Storage and Handling

Store NURTEC ODT at controlled room temperature, 20°C to 25°C (68°F to 77°F); with excursions permitted between 15°C to 30°C (59°F to 86°F) [see USP controlled room temperature].

17 PATIENT COUNSELING INFORMATION

Advise patients to read the FDA-approved patient labeling (Patient Information).

Handling of Orally Disintegrating Tablets Packaging

Instruct patients not to remove the blister from the outer aluminum pouch until ready to use the orally disintegrating tablet inside [see Dosage and Administration (2.3)].

Hypersensitivity Reactions

Inform patients about the signs and symptoms of hypersensitivity reactions and that these reactions can occur days after administration of NURTEC ODT. Advise patients to contact their healthcare provider immediately if signs or symptoms of hypersensitivity reactions occur [see Warnings and Precautions (5.1)].

Hypertension

Inform patients that hypertension can develop or pre-existing hypertension can worsen with NURTEC ODT, and that they should contact their healthcare provider if they experience elevation in their blood pressure [see Warnings and Precautions (5.2)].

Raynaud’s Phenomenon

Inform patients that Raynaud’s phenomenon can develop or worsen with NURTEC ODT. Advise patients to discontinue NURTEC ODT and contact their healthcare provider if they experience signs or symptoms of Raynaud’s phenomenon [see Warnings and Precautions (5.3)].

Pregnancy Registry

There is a pregnancy exposure registry that monitors pregnancy outcomes in women exposed to NURTEC ODT during pregnancy. Encourage participation and advise patients about how they may enroll in the registry [see Use in Specific Populations (8.1)].

This product’s labeling may have been updated. For the most recent Prescribing Information, please visit www.pfizer.com.

LAB-1547-4.0

PATIENT INFORMATION

NURTEC® ODT (NUR-tek)

(rimegepant)

orally disintegrating tablets (ODT), for sublingual or oral use

What is NURTEC ODT?

NURTEC ODT is a prescription medicine used in adults for the:

- acute treatment of migraine attacks with or without aura
- preventive treatment of episodic migraine

It is not known if NURTEC ODT is safe and effective in children.

Do not take NURTEC ODT if you are:

- allergic to rimegepant, NURTEC ODT, or any of the ingredients in NURTEC ODT.

See the end of this leaflet for a complete list of ingredients in NURTEC ODT.

Before you take NURTEC ODT, tell your healthcare provider about all of your medical conditions, including if you:

- have high blood pressure.
- have circulation problems in your fingers and toes.
- have liver problems.
- have kidney problems.
- are pregnant or plan to become pregnant. It is not known if NURTEC ODT will harm your unborn baby. There is a pregnancy exposure registry for women who take NURTEC ODT during pregnancy. The study is named MONITOR (Migraine Observational NURTEC Pregnancy Registry). A registry is a study. The purpose of this registry is to collect information about your health and the health of your baby. Your healthcare provider can help you enroll in this registry. You may also enroll yourself or get more information about the registry by calling 1-877-366-0324, emailing nurtecpregnancyregistry@ppd.com, or by visiting nurtecpregnancyregistry.com.
- are breastfeeding or plan to breastfeed. Very small amounts of NURTEC ODT pass into your breast milk. Talk with your healthcare provider about the best way to feed your baby if you take NURTEC ODT.

Tell your healthcare provider about all the medicines you take, including prescription and over-the-counter medicines, vitamins, and herbal supplements.

How should I take NURTEC ODT?

- Take NURTEC ODT exactly how your healthcare provider tells you to.
- For the acute treatment of migraine attacks when they occur, NURTEC ODT can be taken 1 time each day as needed. You should not take more than 1 tablet in 24 hours.
  - It is not known if it is safe to take more than 18 doses of NURTEC ODT in 30 days.
- For the preventive treatment of episodic migraine, take NURTEC ODT 1 time every other day.
- To take NURTEC ODT:
  - Use dry hands when opening the blister pack.
  - Peel back the foil covering of one blister and gently remove NURTEC ODT. Do not push NURTEC ODT through the foil.
  - As soon as the blister is opened, remove NURTEC ODT and place on or under the tongue.
  - NURTEC ODT will dissolve and no drink or water is needed.
  - Take NURTEC ODT immediately after opening the blister pack. Do not store NURTEC ODT outside the blister pack for future use.
- If you take too much NURTEC ODT, go to the nearest emergency room right away.

What are the possible side effects of NURTEC ODT?

NURTEC ODT may cause serious side effects including:

- Allergic reactions. Allergic reactions, including trouble breathing and rash, can happen after you take NURTEC ODT. This can happen days after you take NURTEC ODT. Call your healthcare provider or get emergency help right away if you have any of the following symptoms, which may be part of an allergic reaction:
  - Swelling of the face, mouth, tongue, or throat
  - Trouble breathing
  - Rash
- High blood pressure. High blood pressure or worsening of high blood pressure can happen after you take NURTEC ODT. Contact your healthcare provider if you have an increase in blood pressure.
- Raynaud’s phenomenon. A type of circulation problem can worsen or happen after you take NURTEC ODT. Raynaud’s phenomenon can lead to your fingers or toes feeling numb, cool, or painful, or changing color from pale, to blue, to red. Contact your healthcare provider if these symptoms occur.

The most common side effect of NURTEC ODT in acute treatment of migraine attacks with or without aura is:

- nausea

The most common side effects of NURTEC ODT in preventive treatment of episodic migraine are:

- nausea
- stomach pain
- indigestion

These are not the only possible side effects of NURTEC ODT.

Call your doctor for medical advice about side effects. You may report side effects to FDA at 1‑800 FDA-1088.

How should I store NURTEC ODT?

- Store NURTEC ODT in the blister package that it comes in.
- Store NURTEC ODT at room temperature between 68°F to 77°F (20°C to 25°C).

Keep NURTEC ODT and all medicines out of the reach of children.

General information about the safe and effective use of NURTEC ODT:

Medicines are sometimes prescribed for purposes other than those listed in a Patient Information leaflet. Do not use NURTEC ODT for a condition for which it was not prescribed. Do not give NURTEC ODT to other people, even if they have the same symptoms that you have. It may harm them. You can ask your pharmacist or healthcare provider for information about NURTEC ODT that is written for health professionals.

What are the ingredients in NURTEC ODT?

Active ingredient in NURTEC ODT: rimegepant

Inactive ingredients in NURTEC ODT: benzyl alcohol, eucalyptol, gelatin, limonene, mannitol, menthol, menthone, menthyl acetate, sucralose, and vanillin

For more information, go to www.nurtec.com or call 1-833-4NURTEC.

LAB-1548-4.0

This Patient Information has been approved by the U.S. Food and Drug Administration Revised: 8/2025

PRINCIPAL DISPLAY PANEL - 75 mg Tablet Blister Pack Carton

NDC 72618-3000-2

NURTEC® ODT
(rimegepant)
orally disintegrating tablets

75 mg PER ORALLY DISINTEGRATING TABLET (ODT)

This package contains 8 ODTs.
Rx Only

PRINCIPAL DISPLAY PANEL - 75 mg NURTEC ODT Blister Pack

PEEL HERE
NURTEC® ODT
(rimegepant) orally
disintegrating
tablets
75 mg
Pfizer Labs Rx only

PRINCIPAL DISPLAY PANEL - 75 mg Tablet Blister Pack Carton SAMPLE

NDC 72618-3001-2
Contains 4 of NDC 72618-3001-1

PROFESSIONAL SAMPLE -
NOT FOR SALE

Rx only

NURTEC® ODT
(rimegepant)
orally disintegrating tablets

75 mg PER ORALLY DISINTEGRATING TABLET

This carton contains 4 blister packs containing 2 orally disintegrating tablets (ODT) each for patient sampling.
Contents in this package are NOT for individual sale. Recommended Dosage: See prescribing information.

PRINCIPAL DISPLAY PANEL - 75 mg Tablet Blister Pack Dosepak SAMPLE

NDC 72618-3001-1

PROFESSIONAL SAMPLE -
NOT FOR SALE

NURTEC® ODT
(rimegepant)
orally disintegrating tablets

75 mg PER ORALLY DISINTEGRATING TABLET (ODT)

This package contains 2 ODTs.

Rx only

PRINCIPAL DISPLAY PANEL - 75 mg NURTEC ODT Blister Pack SAMPLE

PEEL HERE
NURTEC® ODT
(rimegepant) orally
disintegrating tablets
75 mg
PROFESSIONAL SAMPLE -
NOT FOR SALE
LOT Rx only
EXP. YYYY/MM
Pfizer Labs